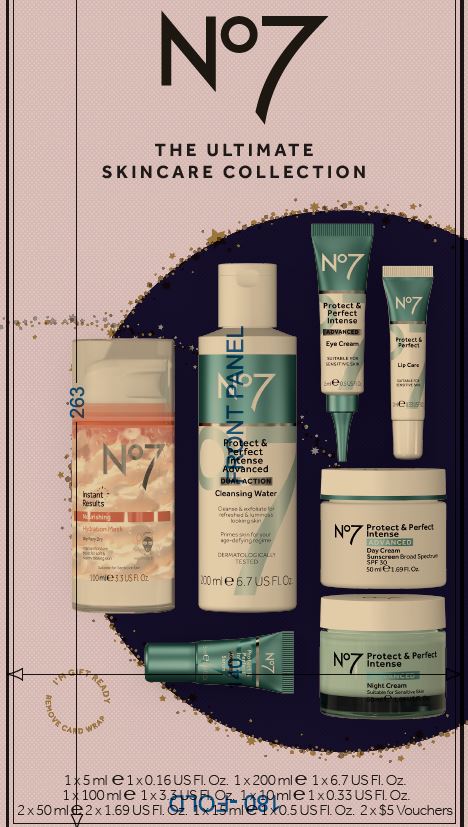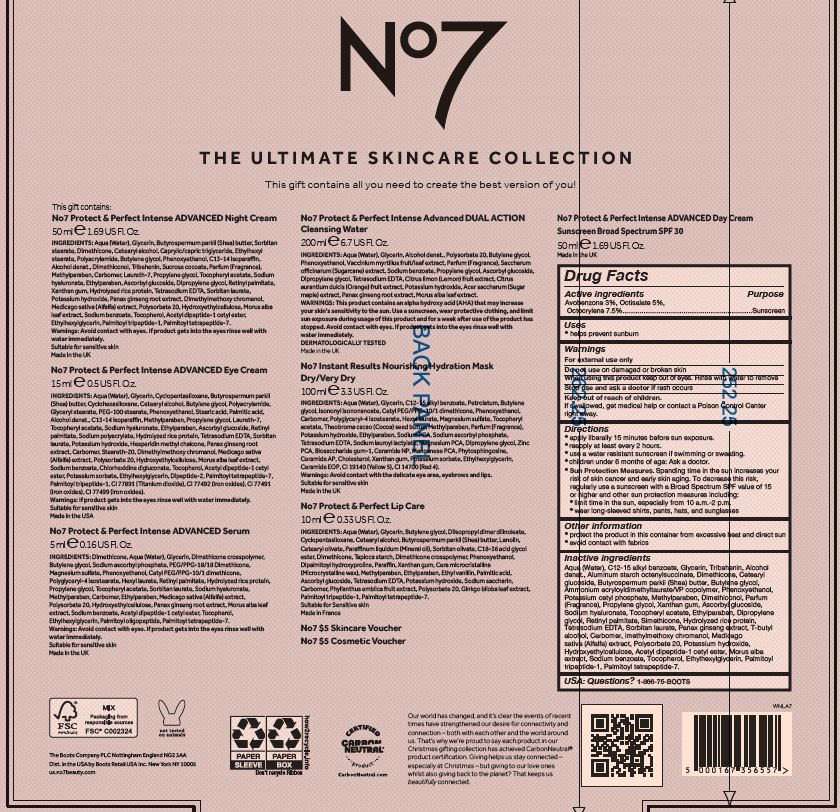 DRUG LABEL: No7 Protect and Perfect Intense Advanced Day Cream SPF 30
NDC: 11489-192 | Form: CREAM
Manufacturer: BCM Ltd
Category: otc | Type: HUMAN OTC DRUG LABEL
Date: 20220624

ACTIVE INGREDIENTS: AVOBENZONE 1.5 g/50 g; OCTOCRYLENE 3.75 g/50 g; OCTISALATE 2.5 g/50 g
INACTIVE INGREDIENTS: WATER; GLYCERIN; DIMETHICONE; CETEARYL GLUCOSIDE; ALUMINUM STARCH OCTENYLSUCCINATE; TRIBEHENIN; POTASSIUM CETYL PHOSPHATE; AMMONIUM ACRYLOYLDIMETHYLTAURATE/VP COPOLYMER; PHENOXYETHANOL; SHEA BUTTER; BUTYLENE GLYCOL; METHYLPARABEN; DIMETHICONOL (40 CST); PROPYLENE GLYCOL; DIPROPYLENE GLYCOL; XANTHAN GUM; ETHYLPARABEN; VITAMIN A PALMITATE; ASCORBYL GLUCOSIDE; EDETATE SODIUM; TERT-BUTYL ALCOHOL; POLYSORBATE 20; DIMETHYLMETHOXY CHROMANOL; POTASSIUM HYDROXIDE; ETHYLHEXYLGLYCERIN; TOCOPHEROL; HYDROXYETHYL CELLULOSE (100 MPA.S AT 2%); MORUS ALBA LEAF; SILICON; PALMITOYL TETRAPEPTIDE-7; SODIUM BENZOATE; PALMITOYL TRIPEPTIDE-1; ALCOHOL; HYALURONATE SODIUM; SORBITAN MONOLAURATE; BUTYLATED HYDROXYTOLUENE; CARBOXYPOLYMETHYLENE; ALFALFA SEED; ASIAN GINSENG

No7 Protect and Perfect Intense Advanced Day Cream Sunscreen Broad Spectrum SPF 30

Carton Active Ingredients Section

Active ingredients

Avobenzone 3%

Octisalate 5%

Octocrylene 7.5%

Uses

Uses - helps prevent sunburn

Warnings

For external use only

Do not use on damaged or broken skin

When using this product keep out of eyes. Rinse with water to remove.

Ask a doctor

Stop use and ask a doctor if rash occurs

Keep out of reach of children

If swallowed, get medical help or contact a Poison Control Center right away.

Directions

apply liberally 15 minutes before sun exposure.

reapply at least every 2 hours.

use a water resistant sunscreen if swimming or sweating.

children under 6 months of age: Ask a doctor.

Sun Protection Measures. Spending time in the sun increases your risk of skin cancer and early skin aging.

To decrease this risk, regularly use a sunscreen with a Broad Spectrum SPF value of 15 or higher and other sun protection measures including:

limit time in the sun, especially from 10 a.m - 2 p.m.

wear long-sleeved shirts,pants,hats and sunglasses

Storage

Other information

protect the product in this container from excessive heat and direct sun

avoid contact with fabrics

Inactive ingredients

Aqua (Water), C12-15 alkyl benzoate, Glycerin, Tribehenin, Alcohol denat., Aluminum starch octenylsuccinate, Dimethicone, Butyrospermum parkii (Shea) butter, Butylene glycol, Ammonium acryloydimethyltaurate/VP copolymer, Cetearyl alcohol, Cetearyl glucoside, Phenoxyethanol, Potassium cetyl phosphate, Methylparaben, Dimethiconol, Parfum (Fragrance), Propylene glycol, Xanthan gum, Ethylparaben, Sodium hyaluronate, Tocopheryl acetate, Ascorbyl glucoside, Dipropylene glycol, Retinyl palmitate, Simethicone, Tetrasodium EDTA, Hydolyzed rice protein, Sorbitan laurate, Panax gingseng root extract, T-butyl alcohol, Carbomer, Dimethylmethoxy chromanol, Medicago sativa (Alfalfa) extract, Polyosorbate 20, Potassium hydroxide, Hydroxyethylcelulose, Acetyl dipeptide-1 cetyl ester, Morus alba leaf extract, Sodium benzoate, Tocopherol, Ethylhexylglycerin, Palmitoyl tripeptide-1, Palmitoyl tetrapeptide-7.

PATIENT COUNSELING INFORMATION

Made in the UK

The Boots Company PLC

Nottingham England NG2 3AA

Dist. in the USA by Boots Retail USA Inc.

New York NY 10005

www.no7beauty.com

Description

No7 THE ULTIMATE SKINCARE COLLECTION

50 ml e 1.69 Fl. Oz.

Box